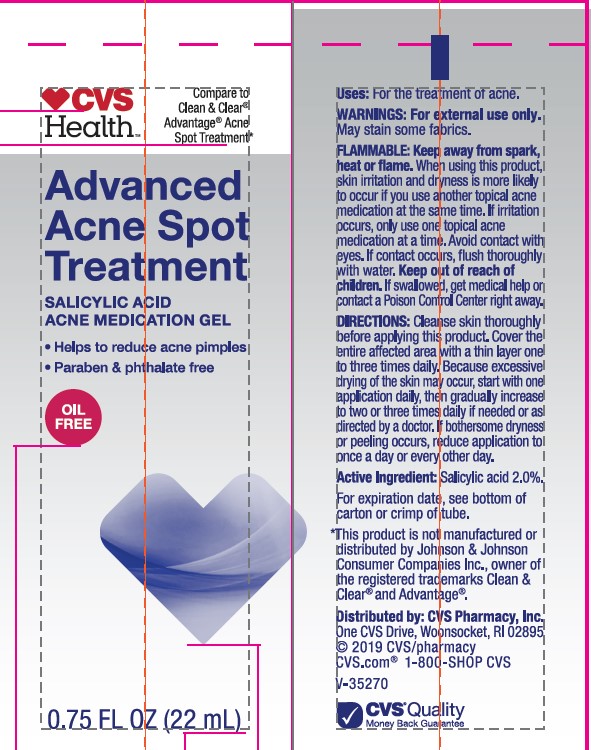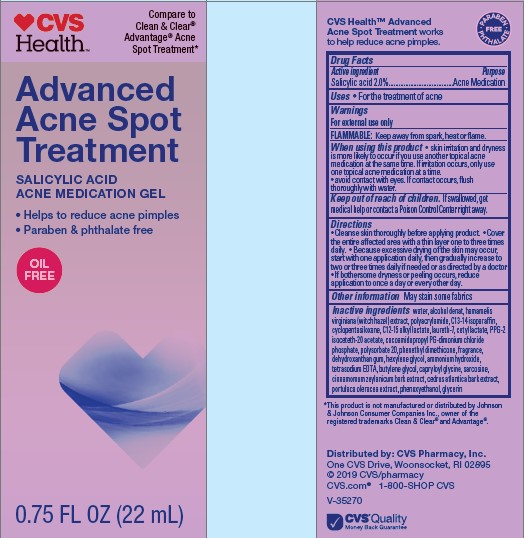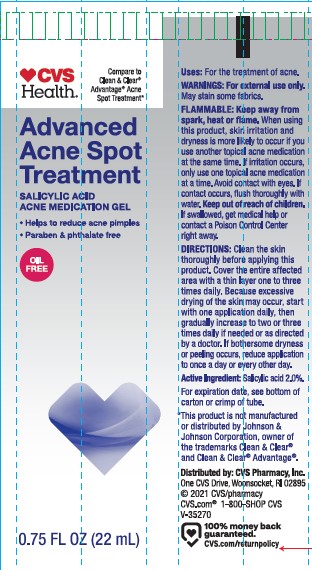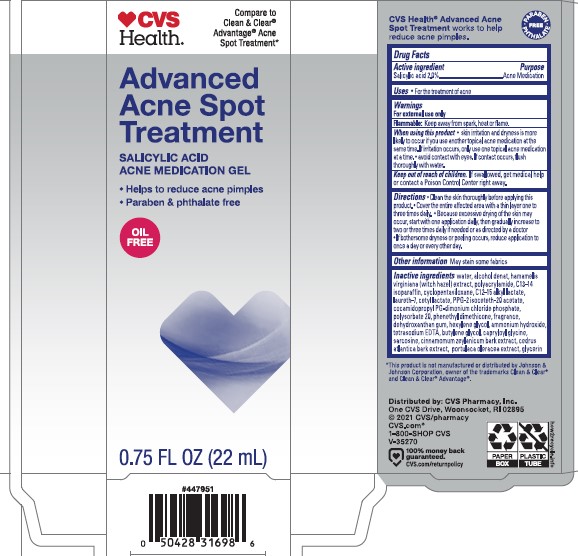 DRUG LABEL: CVS Health Advanced Acne Spot Treatment
NDC: 69842-464 | Form: GEL
Manufacturer: CVS PHARMACY
Category: otc | Type: HUMAN OTC DRUG LABEL
Date: 20241022

ACTIVE INGREDIENTS: SALICYLIC ACID 20 mg/1 mL
INACTIVE INGREDIENTS: POLYACRYLAMIDE (1500 MW); LAURETH-7; ALCOHOL; CINNAMON BARK OIL; PURSLANE; PPG-2 ISOCETETH-20 ACETATE; WATER; BUTYLENE GLYCOL; C12-15 ALKYL LACTATE; C13-14 ISOPARAFFIN; CAPRYLOYL GLYCINE; CEDRUS ATLANTICA BARK; COCAMIDOPROPYL PG-DIMONIUM CHLORIDE PHOSPHATE; DEHYDROXANTHAN GUM; DIMETHICONE; AMMONIA; CETYL LACTATE; GLYCERIN; POLYSORBATE 20; SARCOSINE; EDETATE SODIUM; CYCLOMETHICONE 5; HAMAMELIS VIRGINIANA LEAF

CVS Health Advanced Acne Spot Treatment

Active ingredient

Salicylic acid 2.0%

Purpose

Acne Medication

Uses

- For the treatment of acne

Warnings

For external use only

FLAMMABLE: Keep away from spark, heat, or flame.

When using this product

- skin irritation and dryness is more likely to occur if you use another topical acne medication at the same time. If irritation occurs, only use one topical acne medication at a time.
- avoid contact with eyes. If contact occurs, fluch thoroughly with water.

Keep out of reach of children.

If swallowed, get medical help or contact a Poison Control Center right away. Avoid contact with eyes. If contact occurs, flush thoroughly with water.

Directions

- Cleanse skin thoroughly before applying product.
- Cover the entire afffected area with a thin layer one to three times daily.
- Because excessive drying of the skin may occur, start with one application daily, then gradually increase to two or three times daily if needed or as directed by a doctor
- If bothersome dryness or peeling occurs, reduce application to once a day or every other day.

Other information

May stain some fabrics

Inactive ingredients

water, alcohol denat, hamamelis virginiana (witch hazel) extract, polyacrylamide, C13-14 isoparaffin, glycerin, cyclopentasiloxane, C12-15 alkyl lactate, laureth-7, phenoxyethanol, cetyl lactate, PPG-2 isoceteth-20 acetate, cocamidopropyl PG-dimonium chloride phosphate, polysorbate 20, phenethyl dimethicone, fragrance, dehydroxanthan gum, hexylene glycol, ammonium hydroxide, tetrasodium EDTA, butylene glycol, capryloyl glycine, sarcosine, cinnamomum zeylanicum bark extract, cedrus atlantica bark extract, portulaca oleracea extract